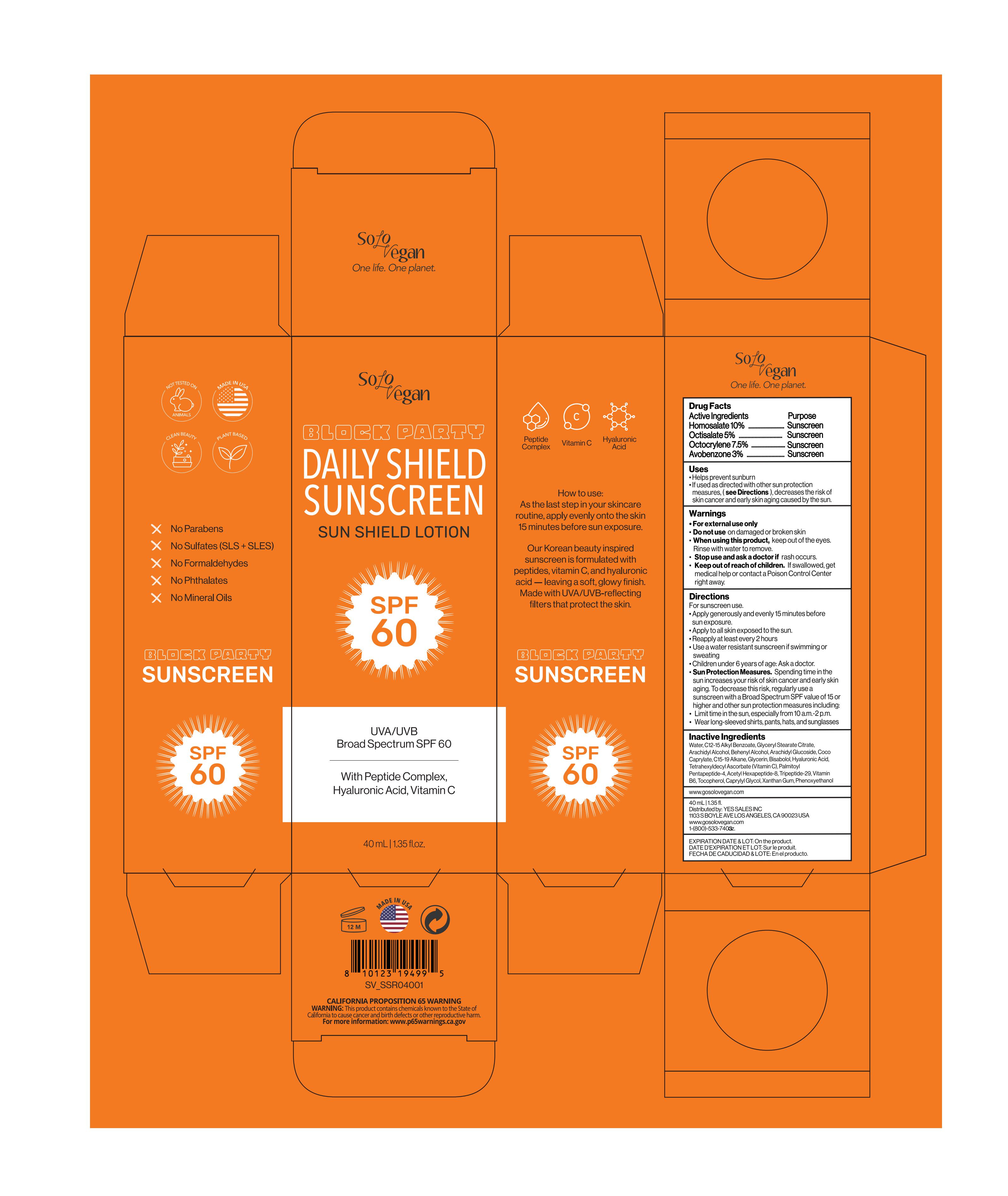 DRUG LABEL: SoloVegan
NDC: 80618-600 | Form: LOTION
Manufacturer: YES SALES INC.
Category: otc | Type: HUMAN OTC DRUG LABEL
Date: 20251111

ACTIVE INGREDIENTS: AVOBENZONE 3 g/100 g; OCTOCRYLENE 7.5 g/100 g; HOMOSALATE 10 g/100 g; OCTISALATE 5 g/100 g
INACTIVE INGREDIENTS: GLYCERIN; HYALURONIC ACID; ARACHIDYL ALCOHOL; WATER; TETRAHEXYLDECYL ASCORBATE; ACETYL HEXAPEPTIDE-8; ALKYL (C12-15) BENZOATE; TOCOPHEROL; CAPRYLYL GLYCOL; BISABOLOL; XANTHAN GUM; C15-19 ALKANE; PALMITOYL PENTAPEPTIDE-4; TRIPEPTIDE-29; PHENOXYETHANOL; BEHENYL ALCOHOL; GLYCERYL STEARATE CITRATE; ARACHIDYL GLUCOSIDE

Warnings

- For external use only
- Do not use on damaged or broken skin
- When using this product, keep out of the eyes. Rinse with water to remove.
- Stop use and ask a doctor if rash occurs
- Keep out of reach of children. If swallowed, get medical help or contact Poison Control Center right away.

Uses

- Helps prevent sunburn
- If used as directed with other sun protection measures, (see Directions), decreases the risk of skin cancer and early skin aging caused by the sun

DOSAGE AND ADMINISTRATION

- For sunscreen use.
- Apply generously and evenly 15 minutes before sun exposure.
- Apply to all skin exposed to the sun
- Reapply at least every 2 hours
- Use a water-resistant sunscreen if swimming or sweating
- Children under 6 years of age: Ask a doctor.
- Sun Protection Measures. Spending time in the sun increases your risk of skin cancer and early skin aging. To decrease this risk, regularly use a sunscreen with a Broad Spectrum SPF value of 15 or higher and other sun protection measures, including:
- Limit time in the sun, especially from 10 a.m.-2 p.m.
- Wear long-sleeved shirts, pants, hats, and sunglasses

INACTIVE INGREDIENT

Water, C12-15 Alkyl Benzoate, Glyceryl Stearate Citrate, Arachidyl Alcohol, Behenyl Alcohol, Arachidyl Glucoside, Coco Caprylate, C15-19 Alkane, Glycerin, Bisabolol, Hyaluronic Acid, Tetrahexyldecyl Ascorbate (Vitamin C), Palmitoyl Pentapeptide-4, Acetyl Hexapeptide-8, Tripeptide-29, Vitamin B6, Tocopherol, Caprylyl Glycol, Xanthan Gum, Phenoxyethanol

OTHER SAFETY INFORMATION

EXPIRATION DATE & LOT: On the product.

DATE D’EXPIRATION ET LOT: Sur le produit.

FECHA DE CADUCIDAD & LOTE: En el producto.

Purpose

Active Ingredients Purpose

Homosalate 10%....................Sunscreen

Octisalate 5%..........................Sunscreen

Octocrylene 7.5%....................Sunscreen

Avobenzone 3%.......................Sunscreen

Keep out of reach of children. If swallowed, get medical help or cotact a Poison Control Center right away.

PACKAGE LABEL

www.gosolovegan.com

40mL | 1.35 fl.

Distributed by: YES SALES INC

1103 S BOYLE AVE LOS ANGELES, CA 90023 USA

www.gosolovegan.com

1-(800)-533-7403oz.

PACKAGE LABEL

51945-4